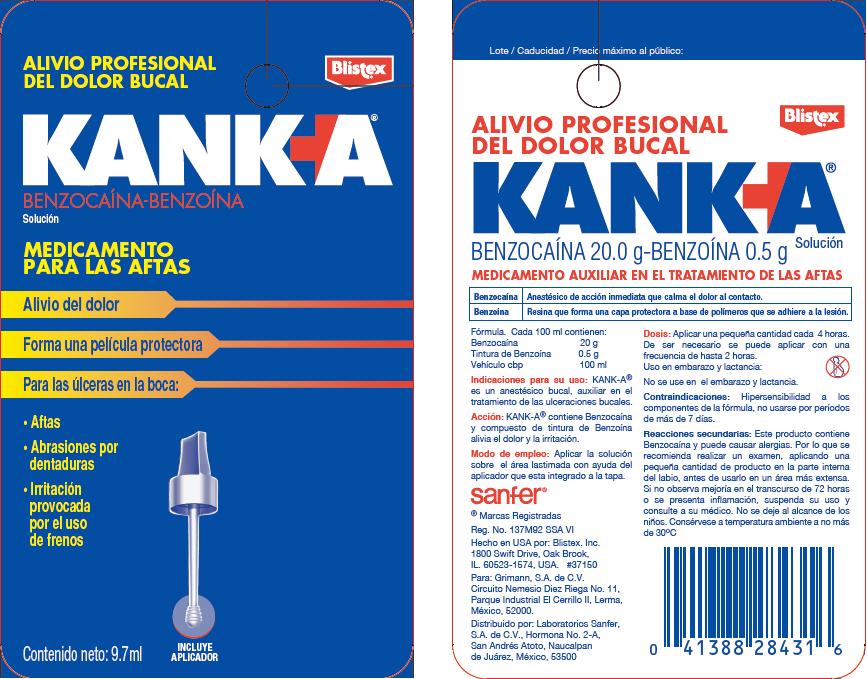 DRUG LABEL: Blistex Kank-A
NDC: 10157-9410 | Form: LIQUID
Manufacturer: Blistex Inc.
Category: otc | Type: HUMAN OTC DRUG LABEL
Date: 20150122

ACTIVE INGREDIENTS: Benzocaine 20 g/100 mL; BENZOIN RESIN 0.5 g/100 mL
INACTIVE INGREDIENTS: ALCOHOL; POLYETHYLENE GLYCOL 300; propylene glycol; tannic acid; dimethyl isosorbide; benzyl alcohol; oleth-10; CASTOR OIL; saccharin; ethylcelluloses; cetylpyridinium chloride

Blistex® Kank-A® Liquid

PURPOSE

Benzocaína | Anestésico de acción inmediata que calma el dolor al contacto.
Benzoína | Resina que forma una capa protectora a base de polímeros que se adhiere a la lesión.

ACTIVE INGREDIENT

INACTIVE INGREDIENT

Fórmula. Cada 100 ml contienen:

Benzocaína | 20 g
Tintura de Benzoína | 0.5 g
Vehículo cbp | 100 ml

Indicaciones para su uso

KANK-A® es un anestésico bucal, auxiliar en el tratamiento de las ulceraciones bucales.

Acción

KANK-A® contiene Benzocaína y compuesto de tintura de Benzoína alivia el dolor y la irritación.

Modo de empleo

Aplicar la solución sobre el área lastimada con ayuda del aplicador que esta integrado a la tapa.

Dosis

Aplicar una pequeña cantidad cada 4 horas. De ser necesario se puede aplicar con una frecuencia de hasta 2 horas.

WARNINGS

Uso en embarazo y lactancia

No se use en el embarazo y lactancia.

Contraindicaciones

Hipersensibilidad a los componentes de la fórmula, no usarse por períodos de más de 7 días.

Reacciones secundarias

Este producto contiene Benzocaína y puede causar alergias. Por lo que se recomienda realizar un examen, aplicando una pequeña cantidad de producto en la parte interna del labio, antes de usarlo en un área más extensa.

STOP USE

Si no observa mejoría en el transcurso de 72 horas o se presenta inflamación, suspenda su uso y consulte a su médico.

KEEP OUT OF REACH OF CHILDREN

No se deje al alcance de los niños.

STORAGE AND HANDLING

Consérvese a temperatura ambiente a no más de 30°C

Distribuido por: Laboratorios Sanfer,
S.A. de C.V., Hormona No. 2-A,
San Andrés Atoto, Naucalpan
de Juárez, México, 53500

PRINCIPAL DISPLAY PANEL - 9.7 mL Bottle Label

ALIVIO PROFESIONAL
DEL DOLOR BUCAL

Blistex®

KANK A®
BENZOCAÍNA-BENZOÍNA
Solución

MEDICAMENTO
PARA LAS AFTAS

Alivio del dolor

Forma una película protectora

Para las úlceras en la boca:

- Aftas
- Abrasiones por
  dentaduras
- Irritación
  provocada
  por el uso
  de frenos

Contenido neto: 9.7ml

INCLUYE
APLICADOR